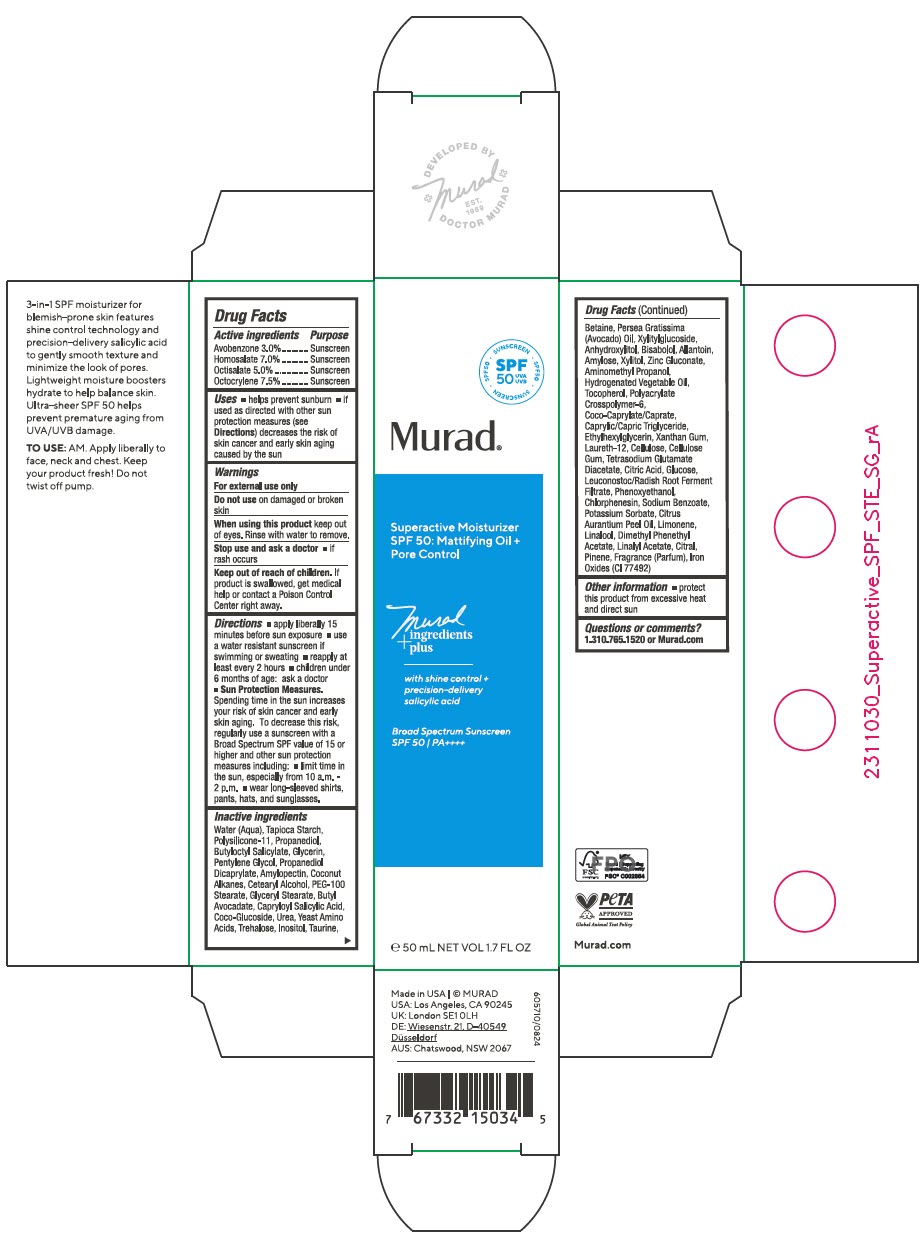 DRUG LABEL: Superactive Moisturizer SPF 50 Mattifying Oil plus Pore Control 
NDC: 70381-133 | Form: CREAM
Manufacturer: Murad, LLC
Category: otc | Type: HUMAN OTC DRUG LABEL
Date: 20250327

ACTIVE INGREDIENTS: AVOBENZONE 3 g/100 mL; HOMOSALATE 7 g/100 mL; OCTISALATE 5 g/100 mL; OCTOCRYLENE 7.5 g/100 mL
INACTIVE INGREDIENTS: WATER; STARCH, TAPIOCA; DIMETHICONE/VINYL DIMETHICONE CROSSPOLYMER (SOFT PARTICLE); PROPANEDIOL; BUTYLOCTYL SALICYLATE; GLYCERIN; PENTYLENE GLYCOL; PROPANEDIOL DICAPRYLATE; AMYLOPECTIN, UNSPECIFIED SOURCE; COCONUT ALKANES; CETOSTEARYL ALCOHOL; PEG-100 STEARATE; GLYCERYL MONOSTEARATE; BUTYL AVOCADATE; CAPRYLOYL SALICYLIC ACID; COCO-GLUCOSIDE; UREA; AMINO ACIDS, SOURCE UNSPECIFIED; TREHALOSE; INOSITOL; TAURINE; BETAINE; AVOCADO OIL; XYLITYLGLUCOSIDE; ANHYDROXYLITOL; LEVOMENOL; ALLANTOIN; AMYLOSE, UNSPECIFIED SOURCE; XYLITOL; ZINC GLUCONATE; AMINOMETHYLPROPANOL; HYDROGENATED AVOCADO OIL; TOCOPHEROL; AMMONIUM ACRYLOYLDIMETHYLTAURATE, DIMETHYLACRYLAMIDE, LAURYL METHACRYLATE AND LAURETH-4 METHACRYLATE COPOLYMER, TRIMETHYLOLPROPANE TRIACRYLATE CROSSLINKED (45000 MPA.S); COCOYL CAPRYLOCAPRATE; MEDIUM-CHAIN TRIGLYCERIDES; ETHYLHEXYLGLYCERIN; XANTHAN GUM; LAURETH-12; POWDERED CELLULOSE; CARBOXYMETHYLCELLULOSE SODIUM, UNSPECIFIED; TETRASODIUM GLUTAMATE DIACETATE; CITRIC ACID MONOHYDRATE; ANHYDROUS DEXTROSE; LEUCONOSTOC/RADISH ROOT FERMENT FILTRATE; PHENOXYETHANOL; CHLORPHENESIN; SODIUM BENZOATE; POTASSIUM SORBATE; BITTER ORANGE OIL; LIMONENE, (+)-; LINALOOL, (+)-; LINALYL ACETATE; CITRAL; PINENE; FERRIC OXIDE YELLOW; DIMETHYL BENZYL CARBINYL ACETATE

Superactive Moisturizer SPF 50: Mattifying Oil + Pore Control
SPF 50

Drug Facts

ACTIVE INGREDIENT

Active ingredients | Purpose
Avobenzone 3.0% | Sunscreen
Homosalate 7.0% | Sunscreen
Octisalate 5.0% | Sunscreen
Octocrylene 7.5% | Sunscreen

Uses

- helps prevent sunburn
- if used as directed with other sun protection measures (see Directions) decreases the risk of skin cancer and early skin aging caused by the sun

Warnings

For external use only

Do not use on damaged or broken skin

When using this product keep out of eyes. Rinse with water to remove.

Stop use and ask a doctor

- if rash occurs

Keep out of reach of children. If product is swallowed, get medical help or contact a Poison Control Center right away.

Directions

- apply liberally 15 minutes before sun exposure
- use a water resistant sunscreen if swimming or sweating
- reapply at least every 2 hours
- children under 6 months of age: ask a doctor
- Sun Protection Measures. Spending time in the sun increases your risk of skin cancer and early skin aging. To decrease this risk, regularly use a sunscreen with a Broad Spectrum SPF value of 15 or higher and other sun protection measures including:
  - limit time in the sun, especially from 10 a.m. - 2 p.m.
  - wear long-sleeved shirts, pants, hats, and sunglasses.

Inactive ingredients

Water (Aqua), Tapioca Starch, Polysilicone-11, Propanediol, Butyloctyl Salicylate, Glycerin, Pentylene Glycol, Propanediol Dicaprylate, Amylopectin, Coconut Alkanes, Cetearyl Alcohol, PEG-100 Stearate, Glyceryl Stearate, Butyl Avocadate, Capryloyl Salicylic Acid, Coco-Glucoside, Urea, Yeast Amino Acids, Trehalose, Inositol, Taurine, Betaine, Persea Gratissima (Avocado) Oil, Xylitylglucoside, Anhydroxylitol, Bisabolol, Allantoin, Amylose, Xylitol, Zinc Gluconate, Aminomethyl Propanol, Hydrogenated Vegetable Oil, Tocopherol, Polyacrylate Crosspolymer-6, Coco-Caprylate/Caprate, Caprylic/Capric Triglyceride, Ethylhexylglycerin, Xanthan Gum, Laureth-12, Cellulose, Cellulose Gum, Tetrasodium Glutamate Diacetate, Citric Acid, Glucose, Leuconostoc/Radish Root Ferment Filtrate, Phenoxyethanol, Chlorphenesin, Sodium Benzoate, Potassium Sorbate, Citrus Aurantium Peel Oil, Limonene, Linalool, Dimethyl Phenethyl Acetate, Linalyl Acetate, Citral, Pinene, Fragrance (Parfum), Iron Oxides (CI 77492)

Other information

- protect this product from excessive heat and direct sun

Questions or comments?

1.310.765.1520 or Murad.com

PRINCIPAL DISPLAY PANEL - 50 mL Bottle Carton

SPF
50
UVA
UVB

• SUNSCREEN • SPF50 • SUNSCREEN • SPF50

Murad®

Superactive Moisturizer
SPF 50: Mattifying Oil +
Pore Control

Murad
ingredients
+ plus

with shine control +
precision-delivery
salicylic acid

Broad Spectrum Sunscreen
SPF 50 / PA++++

℮ 50 mL NET VOL 1.7 FL OZ